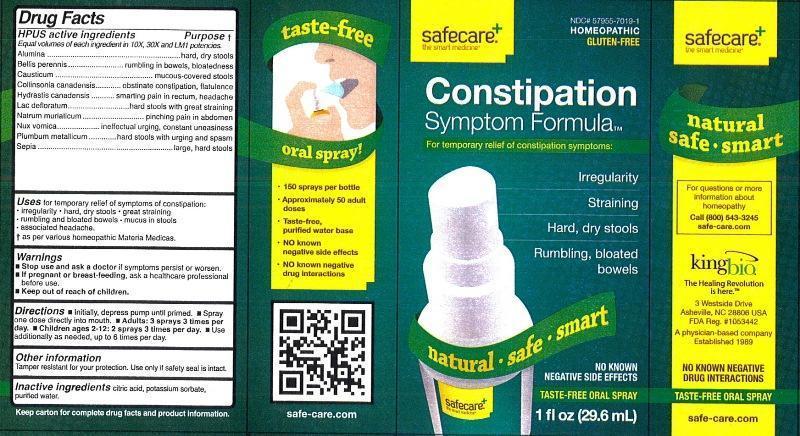 DRUG LABEL: Constipation Symptom Formula
NDC: 57955-7019 | Form: LIQUID
Manufacturer: King Bio Inc.
Category: homeopathic | Type: HUMAN OTC DRUG LABEL
Date: 20130220

ACTIVE INGREDIENTS: ALUMINUM OXIDE 10 [hp_X]/29.6 mL; BELLIS PERENNIS 10 [hp_X]/29.6 mL; CAUSTICUM 10 [hp_X]/29.6 mL; COLLINSONIA CANADENSIS ROOT 10 [hp_X]/29.6 mL; GOLDENSEAL 10 [hp_X]/29.6 mL; SKIM MILK 10 [hp_X]/29.6 mL; SODIUM CHLORIDE 10 [hp_X]/29.6 mL; STRYCHNOS NUX-VOMICA SEED 10 [hp_X]/29.6 mL; LEAD 10 [hp_X]/29.6 mL; SEPIA OFFICINALIS JUICE 10 [hp_X]/29.6 mL
INACTIVE INGREDIENTS: WATER; POTASSIUM SORBATE; CITRIC ACID MONOHYDRATE

Constipation Symptom Formula

Active Ingredients

HPUS Active ingredients

Equal volumes of each ingredient in 10X, 30X and LM1 potencies.

Alumina, Bellis perennis, Causticum, Collinsonia canadensis, Hydrastis canadensis, Lac defloratum, Natrum muriaticum, Nux vomica, Plumbum metallicum, Sepia

Inactive Ingredients: Citric acid, potassium sorbate, purified water.

Purpose

HPUS active ingredients Purpose†

Equal volumes of each ingredient in 10X, 30X, and LM1 potencies.

Alumina...........................................................................hard, dry stools

Bellis perennis................................................................rumbling in bowels, bloatedness

Causticum......................................................................mucous-covered stools

Collinsonia canadensis..................................................obstinate constipation, flatulence

hydrastis canadensis.....................................................smarting pain in rectum, headache

Lac defloratum...............................................................hard stools with great straining

Natrum muriaticum........................................................pinching pain in abdomen

Nux vomica....................................................................ineffectual urging, constant uneasiness

plumbum metallicum......................................................hard stools with urging and spasm

Sepia.............................................................................large, hard stools

Indications and Usage

Uses for temporary relief of symptoms of constipation:

- irregularity
- hard, dry stools
- great straining
- rumbling and bloated bowels
- mucus in stools
- associated headache

† as per various homeopathic Materia Medicas.

Warnings

- Stop use and ask a doctor if symptoms persist or worsen.
- If pregnant or breast-feeding, ask a healthcare professional before use.
- Keep out of reach of children.

Other Information

Tamper resistant for your protection. Use only if safety seal is intact.

Keep out of reach of children.

Dosage and Administration

Directions:

- Initially, depress pump until primed.
- Spray one dose directly into mouth
- Adults (12 and up): 3 sprays 3 times per day.
- Use additionally as needed, up to 6 times per day.

PACKAGE LABEL

King Bio Inc.

3 Westside Drive

Asheville, NC 28806

For questions or more information about homeopathy

Call (800) 543-3245 or safe-care.com